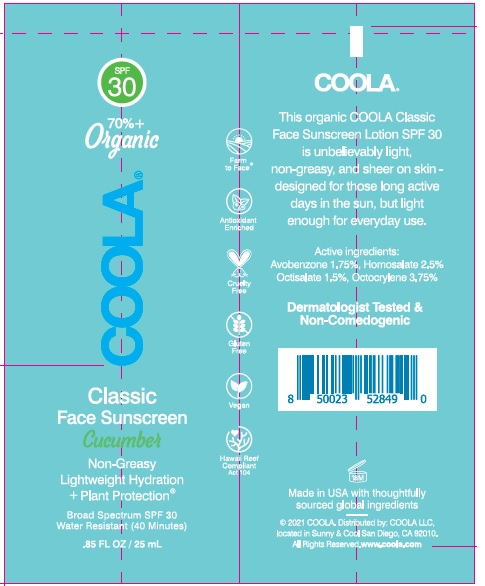 DRUG LABEL: COOLA CLASSIC FACE SUNSCREEN Cucumber Broad Spectrum
NDC: 79753-073 | Form: LOTION
Manufacturer: COOLA LLC
Category: otc | Type: HUMAN OTC DRUG LABEL
Date: 20241227

ACTIVE INGREDIENTS: AVOBENZONE 1.75 g/100 mL; HOMOSALATE 2.5 g/100 mL; OCTISALATE 1.5 g/100 mL; OCTOCRYLENE 3.75 g/100 mL
INACTIVE INGREDIENTS: ALOE VERA LEAF; AMYRIS BALSAMIFERA OIL; BRASSICA RAPA SUBSP. OLEIFERA OIL; BUTYLENE GLYCOL; CAMELINA SATIVA SEED OIL; CAPRYLYL GLYCOL; CARTHAMUS TINCTORIUS SEED OLEOSOMES; SAFFLOWER OIL; CETOSTEARYL ALCOHOL; CETYL PALMITATE; CITRIC ACID MONOHYDRATE; CITRONELLYL ACETATE; ORANGE OIL; DECANAL; DECYL GLUCOSIDE; DIMETHICONE; 2,6-DIMETHYL-5-HEPTENAL; GLYCERIN; 1,2-HEXANEDIOL; 3-HEXEN-1-OL, (3Z)-; HEXENYL ACETATE, (2Z)-; HEXYL ACETATE; HYDROLYZED JOJOBA ESTERS (ACID FORM); JOJOBA OIL, RANDOMIZED; MEADOWFOAM SEED OIL; LINALYL ACETATE; MAURITIA FLEXUOSA FRUIT OIL; METHYL DIHYDROABIETATE; NEROL; OPUNTIA FICUS-INDICA WHOLE; AMMONIUM ACRYLOYLDIMETHYLTAURATE, DIMETHYLACRYLAMIDE, LAURYL METHACRYLATE AND LAURETH-4 METHACRYLATE COPOLYMER, TRIMETHYLOLPROPANE TRIACRYLATE CROSSLINKED (45000 MPA.S); DIMETHICONE/VINYL DIMETHICONE CROSSPOLYMER (SOFT PARTICLE); RASPBERRY SEED OIL; SILICON DIOXIDE; DISODIUM PHTHALATE; SORBITAN MONOOLEATE; SORBITAN MONOPALMITATE; SQUALANE; TRIETHYL CITRATE; TROPOLONE; WATER; XANTHAN GUM

COOLA CLASSIC FACE SUNSCREEN Cucumber Broad Spectrum SPF 30

DRUG FACTS

Active Ingredients
Avobenzone 1.75% Homosalate 2.5%
Octisalate 1.5% Octocrylene 3.75%

Purpose
Sunscreen

Uses
• helps prevent sunburn • if used as directed with
other sun protection measures (see Directions)
decreases the risk of skin cancer and early skin
aging caused by the sun.

Warnings
For external use only.

Do not use on damaged or broken skin.

When using this product keep out of eyes.
Rinse with water to remove.

Stop use and ask doctor if rash occurs.

Keep out of reach of children. If product is swallowed
get medical help or contact a Poison Control Center right away.

Directions
• apply liberally 15 minutes before sun exposure
• reapply:
• after 40 minutes of swimming or sweating
• immediately after towel drying
• at least every 2 hours
• Sun Protection Measures. Spending time in the sun
increases your risk of skin cancer and early skin aging. To
decrease this risk, regularly use a sunscreen with a broad
spectrum SPF of 15 or higher and after sun protection.
measures including:
• limit time in the sun, especially from 10 a.m. – 2 p.m.
• wear long-sleeve shirts, pants, hats, and sunglasses.
• Children under 6 months: Ask a doctor

Inactive Ingredients
Aloe Barbadensis Leaf Juice (ORGANIC), Amyris
Balsamifera Bark Oil*, Brassica Campestris
(Rapeseed) Seed Oil, Butylene Glycol, Camelina
Sativa Seed Oil, Caprylyl Glycol, Carthamus
Tinctorius (Safflower) Oleosomes, Carthamus
Tinctorius (Safflower) Seed Oil (ORGANIC),
Cetearyl Alcohol, Cetyl Palmitate, Citric Acid,
Citronellyl Acetate*, Citrus Aurantium Dulcis
(Orange) Peel Oil*, Decanal*, Decyl Glucoside,
Dimethicone, Dimethyl Heptenal*, Glycerin
(ORGANIC), 1,2-Hexanediol, 3-Hexenol*,
Hexenyl Acetate*, Hexyl Acetate*, Hydrolyzed
Jojoba Esters, Jojoba Esters, Limnanthes Alba
(Meadowfoam) Seed Oil, Linalyl Acetate*,
Mauritia Flexuosa (Buriti) Fruit Oil, Methyl
Dihydroabietate, Nerol*, Opuntia Ficus-Indica
Flower Extract, Polyacrylate, Crosspolymer-6,
Polysilicone-11, Rubus Idaeus (Raspberry) Seed
Oil, Silica, Sodium Phytate, Sorbitan Oleate,
Sorbitan Palmitate, Squalane, Triethyl Citrate*,
Tropolone, Water, Xanthan Gum

Other Information

- protect this product from excessive heat and direct sun

Questions or Comments? Call 760-940-2125

Package Label - COOLA CLASSIC FACE SUNSCREEN Cucumber Broad Spectrum SPF 30

NEEDS OUTER BOX LABELING INSERTED

SPF
30

70% +
Organic

COOLA®

Classic
Face Sunscreen
Cucumbar

Non-Greasy
Ultralight Hydration
+Plant Protection®

Broad Spectrum SPF 30
Water Resistant (40 Minutes)

.85 FL OZ / 25 mL

2021 COOLA. Distributed by: COOLA LLC,
located in Sunny & Cool San Diego, CA 92010. ,
All Rights Reserved. www.coola.com

Box TO DELETE OLD!!!!!!

Tube

res